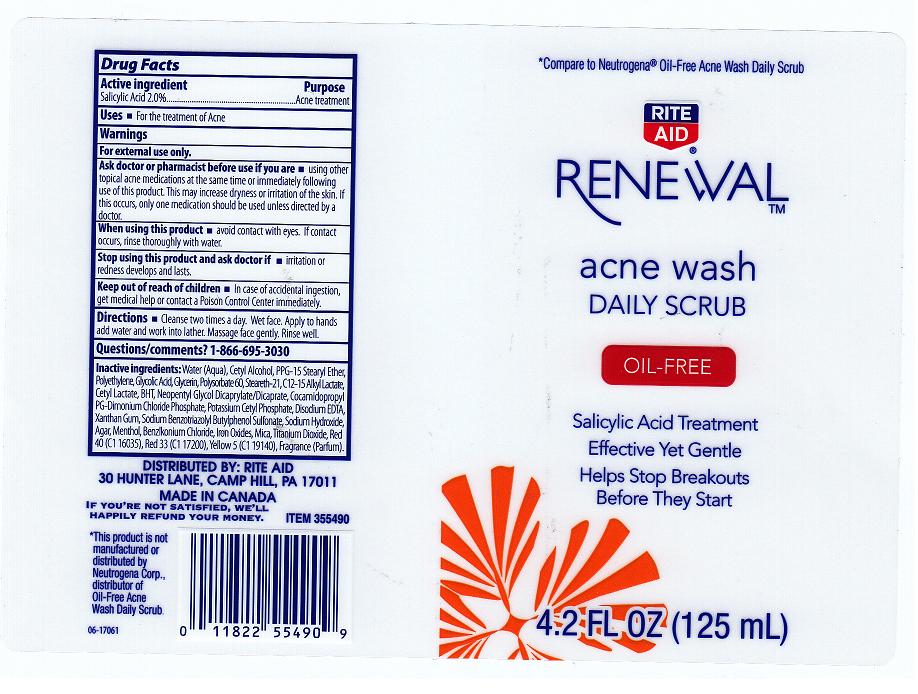 DRUG LABEL: RITE AID RENEWAL
NDC: 11822-8210 | Form: CREAM
Manufacturer: RITE AID CORPORATION
Category: otc | Type: HUMAN OTC DRUG LABEL
Date: 20110729

ACTIVE INGREDIENTS: SALICYLIC ACID 2 mL/100 mL
INACTIVE INGREDIENTS: WATER; CETYL ALCOHOL; STEARETH-15; POLYETHYLENE GLYCOLS; GLYCOLIC ACID; GLYCERIN; POLYSORBATE 60; STEARETH-21; BUTYLATED HYDROXYTOLUENE; NEOPENTYL GLYCOL DICAPRATE; COCAMIDOPROPYL PG-DIMONIUM CHLORIDE PHOSPHATE; POTASSIUM CETYL PHOSPHATE; EDETATE DISODIUM; XANTHAN GUM; SODIUM HYDROXIDE; AGAR; MENTHOL; BENZALKONIUM CHLORIDE; FERRIC OXIDE RED; MICA; TITANIUM DIOXIDE; FD&C RED NO. 40; D&C RED NO. 33; FD&C YELLOW NO. 5

DRUG FACTS

ACTIVE INGREDIENT

SALICYLIC ACID 2.0%

PURPOSE

ACNE TREATMENT

USES

For the treatment of Acne

WARNINGS

FOR EXTERNAL USE ONLY

ASK DOCTOR OR PHARMACIST BEFORE USE IF YOU ARE

USING OTHER TOPICAL ACNE MEDICATIONS AT THE SAME TIME OR IMMEDIATELY FOLLOWING USE OF THIS PRODUCT. THIS MAY INCREASE DRYNESS OR IRRITATION OF THE SKIN. IF THIS OCCURS, ONLY ONE MEDICATION SHOULD BE USED UNLESS DIRECTED BY A DOCTOR.

WHEN USING THIS PRODUCT

AVOID CONTACT WITH EYES. IF CONTACT OCCURS, RINSE THOROUGHLY WITH WATER.

STOP USING THIS PRODUCT AND ASK DOCTOR IF

IRRITATION OR REDNESS DEVELOPS AND LASTS

KEEP OUT OF REACH OF CHILDREN

IN CASE OF ACCIDENTAL INGESTION, GET MEDICAL HELP OR CONTACT POISON CONTROL CENTER IMMEDIATELY.

DIRECTIONS

CLEANSE TWO TIMES A DAY. WET FACE. APPLY TO HANDS ADD WATER AND WORK INTO LATHER. MASSAGE FACE GENTLY. RINSE WELL.

QUESTIONS OR COMMENTS

1-866-695-3030

INACTIVE INGREDIENTS

WATER, CETYL ALCOHOL, PPG-15 STEARYL ETHER, POLYETHYLENE, GLYCOLIC ACID, GLYCERIN, POLYSORBATE 60, STEREATH-21, C12-15 ALKYL LACTATE, CETYL LACTATE, BHT, NEOPENTYL GLYCOL DICAPRYLATE/DICAPRATE, COCAMIDOPROPYL PG-DIMONIUM CHLORIDE PHOSPHATE, POTASSIUM CETYL PHOSPHATE, DISODIUM EDTA, XANTHAN GUM, SODIUM BENZOTRIAZOLYL BUTYLPHENOL SULFONATE, SODIUM HYDROXIDE, AGAR, MENTHOL, BENZALKONIUM CHLORIDE, MICA, TITANIUM DIOXIDE, RED 40 (CI 16035), RED 33 (CI 17200), YELLOW 5 (CI 19140), FRAGRANCE (PARFUM)